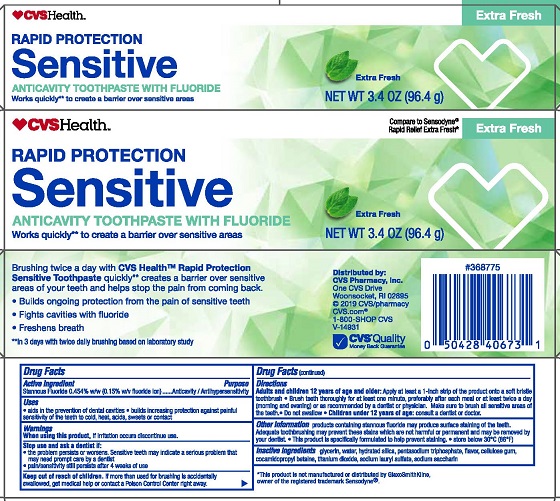 DRUG LABEL: CVS Rapid Protection Sensitive
NDC: 69842-252 | Form: PASTE, DENTIFRICE
Manufacturer: CVS Pharmacy
Category: otc | Type: HUMAN OTC DRUG LABEL
Date: 20251112

ACTIVE INGREDIENTS: STANNOUS FLUORIDE 0.15 g/100 g
INACTIVE INGREDIENTS: WATER; SACCHARIN SODIUM; TITANIUM DIOXIDE; SODIUM LAURYL SULFATE; GLYCERIN; HYDRATED SILICA; COCAMIDOPROPYL BETAINE; SODIUM TRIPOLYPHOSPHATE ANHYDROUS; CARBOXYMETHYLCELLULOSE SODIUM, UNSPECIFIED FORM

5820006 CVS Rapid Protection Sensitive Toothpaste

Drug Facts

Active ingredient

Stannous fluoride 0.454% (0.15% w/v fluoride ion)

Purpose

Anticavity / Antihypersensitivity

Uses

- aids in the prevention of dental cavities
- builds increasing protection against painful sensitivity of the teeth to cold, heat, acids, sweets or contact

Warnings

When using this product, if irritation occurs discontinue use.

Stop use and ask a dentist if:

- the problem persists or worsens. Sensitive teeth may indicate a serious problem that may need prompt care by a dentist.
- pain/sensitivity still persists after 4 weeks of use

Keep out of reach of children. If more than used for brushing is accidentally swallowed, get medical help or contact a Poison Control Center right away.

Directions

Adults and children 12 years of age and older: Apply at least a 1-inch strip of the product onto a soft bristle toothbrush.

- Brush teeth thoroughly for at least one minute, preferably after each meal or at least twice a day (morning and evening) or as recommended by a dentist or physican.
- Make sure to brush all sensitive areas of the teeth.
- Do not swallow
- Children under 12 years of age: consult a dentist or doctor

Other information

products containing stannous fluoride may produce surface staining of the teeth. Adequate toothbrushing may prevent these stains which are not harmful or permanent and may be removed your dentist.

- This product is specifically formulated to help prevent staining
- store below 30°C (86°F)

INACTIVE INGREDIENT

Inactive ingredients glycerin, water, hydrated silica, pentasodium triphosphate, flavor, cellulose gum, cocamidopropyl betaine, titanium dioxide, sodium lauryl sulfate, sodium saccharin

** in 3 days with twice daily brushing based on laboratory study

Distributed by:

CVS Pharmacy, Inc.

One CVS Drive

Woonsocket, RI 02895

CVS.com®

1-800-SHOP CVS

PACKAGE LABEL

CVS Health™

RAPID PROTECTION

SENSITIVE

ANTICAVITY TOOTHPASTE WITH FLUORIDE

Works quickly** to create a barrier over sensitive areas

Extra Fresh

NET WT 3.4 OZ (96.4 g)